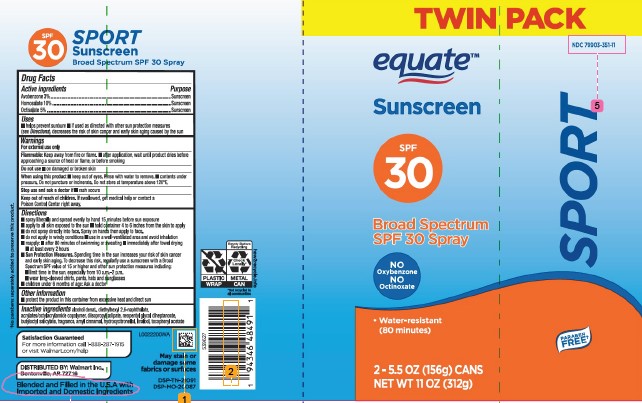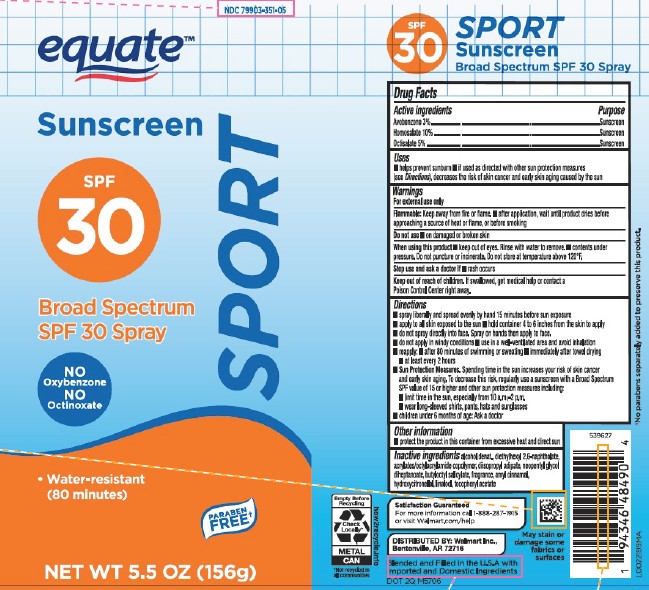 DRUG LABEL: Avobenzone, Homosalate, Octisalate
NDC: 79903-351 | Form: SPRAY
Manufacturer: Walmart Inc.
Category: otc | Type: HUMAN OTC DRUG LABEL
Date: 20260227

ACTIVE INGREDIENTS: HOMOSALATE 100 mg/1 g; OCTISALATE 50 mg/1 g; AVOBENZONE 30 mg/1 g
INACTIVE INGREDIENTS: ALCOHOL; DIETHYLHEXYL 2,6-NAPHTHALATE; ACRYLATE/ISOBUTYL METHACRYLATE/N-TERT-OCTYLACRYLAMIDE COPOLYMER (40000 MW); DIISOPROPYL ADIPATE; NEOPENTYL GLYCOL DIHEPTANOATE; BUTYLOCTYL SALICYLATE; .ALPHA.-AMYLCINNAMALDEHYDE; HYDROXYCITRONELLAL; LINALOOL, (+/-)-; .ALPHA.-TOCOPHEROL ACETATE

Equate D41.000/D41AA
Sport Sunscreen Spray SPF 30

Claims

SFP 30

SPORT

SUNSCREEN

Broad Spectrum SPF 30 Spray

ACTIVE INGREDIENTS

Avobenzone 3%
Homosalate 10%
Octisalate 5%

PURPOSE

Sunscreen

Uses

- helps prevent sunburn
- if used as directed with other sun protection measures (see Directions), decreases the risk of skin cancer and early skin aging caused by the sun

Warnings

for this product

Flammable

Keep away from fire or flame.

- after application, wait until product dries before approaching a source of heat or flame, or before smoking

Do not use

- on damaged or broken skin

When using this product

- keep out of eyes. Rinse with water to remove.
- contents under pressure. Do not puncture or incinerate. Do not store at temperature above 120ºF.

Stop use and ask a doctor if

- rash occurs

Keep out of reach of children.

If swallowed, get medical help or contact a Poison Control Center right away.

Directions

- spray liberally and spread evenly by hand 15 minutes before sun exposure
- apply to all skin exposed to the sun
- hold container 4 to 6 inches from the skin to apply
- do not spray directly into face. Spray on hands then apply to face.
- do not apply in windy conditions
- use in a well-ventilated area and avoid inhalation
- reapply:
- after 80 minutes of swimming or sweating
- immediately after towel drying
- at least every 2 hours
- Sun Protection Measures.Spending time in the sun increases your risk of skin cancer and early skin aging. To decrease this risk, regularly use a sunscreen with a Broad Spectrum SPF value of 15 or higher and other sun protection measures including:
- limit time in the sun, especially from 10 a.m.–2 p.m.
- wear long-sleeved shirts, pants, hats and sunglasses
- children under 6 months of age: Ask a doctor

Other information

- protect the product in this container from excessive heat and direct sun

INACTIVE INGREDIENTS

alcohol denat., diethylhexyl 2,6-naphthalate, acrylates/octylacrylamide copolymer, diisopropyl adipate, neopentyl glycol diheptanoate, butyloctyl salicylate, fragrance, amyl cinnamal, hydroxycitronellal, linalool, tocopheryl acetate

ADVERSE REACTION

Satisfaction Guaranteed

For more information call 1-888-287-1915 or visit Walmart.com/help

DISTRIBUTED BY: Walmart Inc.,

Bentonville, AR 72716

Blended and Filled in the U.S.A. with imported and Domestic Ingredients

Empty Before Recycling

Check Locally*

METAL CAN

hot2recycle.info

*Not recycled in all communities

Disclaimers

May stain or damage some fabrics or surfaces

†No parabens separately added to preserve this product.

PRINCIPAL DISPLAY PANEL

NDC 79903-351-05

equate™

Sunscreen

SPF 30

SPORT

Broad Spectrum

SPF 30 Spray

NO Oxybenzone

NO Octinoxate

- Water-resistant (80 minutes)

PARABEN FREE†

NET WT 5.5 OZ (156 g)

PRINCIPAL DISPLAY PANEL

TWIN PACK

NDC 79903-351-11

equate™

Sunscreen

SPF 30

SPORT

Broad Spectrum

SPF 30 Spray

NO Oxybenzone

NO Octinoxate

- Water-resistant (80 minutes)

PARABEN FREE†

2 - 5.5 OZ (156 g) CANS

NET WT 11 OZ (312 g)